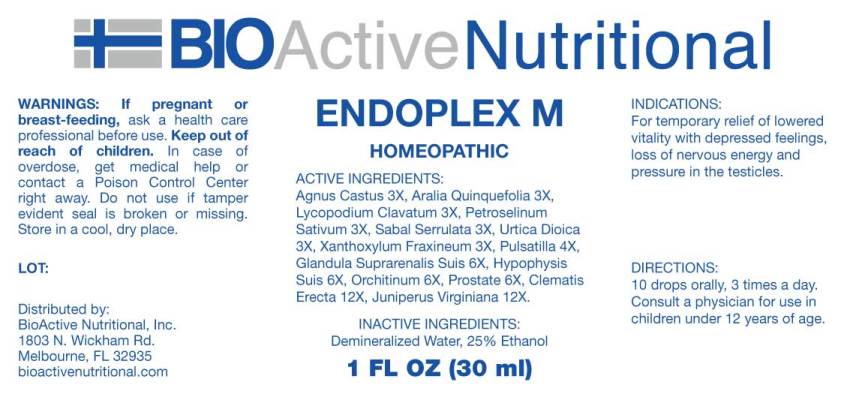 DRUG LABEL: Endoplex M
NDC: 43857-0508 | Form: LIQUID
Manufacturer: BioActive Nutritional, Inc
Category: homeopathic | Type: HUMAN OTC DRUG LABEL
Date: 20241017

ACTIVE INGREDIENTS: CHASTE TREE 3 [hp_X]/1 mL; AMERICAN GINSENG 3 [hp_X]/1 mL; LYCOPODIUM CLAVATUM SPORE 3 [hp_X]/1 mL; PETROSELINUM CRISPUM WHOLE 3 [hp_X]/1 mL; SAW PALMETTO 3 [hp_X]/1 mL; URTICA DIOICA WHOLE 3 [hp_X]/1 mL; ZANTHOXYLUM AMERICANUM BARK 3 [hp_X]/1 mL; PULSATILLA VULGARIS WHOLE 4 [hp_X]/1 mL; SUS SCROFA ADRENAL GLAND 6 [hp_X]/1 mL; SUS SCROFA TESTICLE 6 [hp_X]/1 mL; SUS SCROFA PITUITARY GLAND 6 [hp_X]/1 mL; SUS SCROFA PROSTATE 6 [hp_X]/1 mL; CLEMATIS RECTA FLOWERING TOP 12 [hp_X]/1 mL; JUNIPERUS VIRGINIANA TWIG 12 [hp_X]/1 mL
INACTIVE INGREDIENTS: WATER; ALCOHOL

DRUG FACTS:

ACTIVE INGREDIENTS:

Agnus Castus 3X, Aralia Quinquefolia 3X, Lycopodium Clavatum 3X, Petroselinum Sativum 3X, Sabal Serrulata 3X, Urtica Dioica 3X, Xanthoxylum Fraxineum 3X, Pulsatilla (Vulgaris) 4X, Glandula Suprarenalis Suis 6X, Hypophysis Suis 6X, Orchitinum (Suis) 6X, Prostate (Suis) 6X, Clematis Erecta 12X, Juniperus Virginiana 12X.

INDICATIONS:

For temporary relief of lowered vitality with depressed feelings, loss of nervous energy and pressure in the testicles.

WARNINGS:

If pregnant or breast-feeding, ask a health care professional before use.

Keep out of reach of children. In case of overdose, get medical help or contact a Poison Control Center right away.

Do not use if tamper evident seal is broken or missing.

Store in cool, dry place.

Keep out of reach of children. In case of overdose, get medical help or contact a Poison Control Center right away.

DIRECTIONS:

10 drops orally, 3 times a day. Consult a physician for use in children under 12 years of age.

INDICATIONS:

For temporary relief of lowered vitality with depressed feelings, loss of nervous energy and pressure in the testicles.

INACTIVE INGREDIENTS:

Demineralized Water, 25% Ethanol

QUESTIONS:

Distributed by:
BioActive Nutritional, Inc.
1803 N. Wickham Rd.
Melbourne, FL 32935
bioactivenutritional.com

PACKAGE LABEL DISPLAY:

BIOActive Nutritional

ENDOPLEX M

HOMEOPATHIC

1 FL OZ (30 ml)